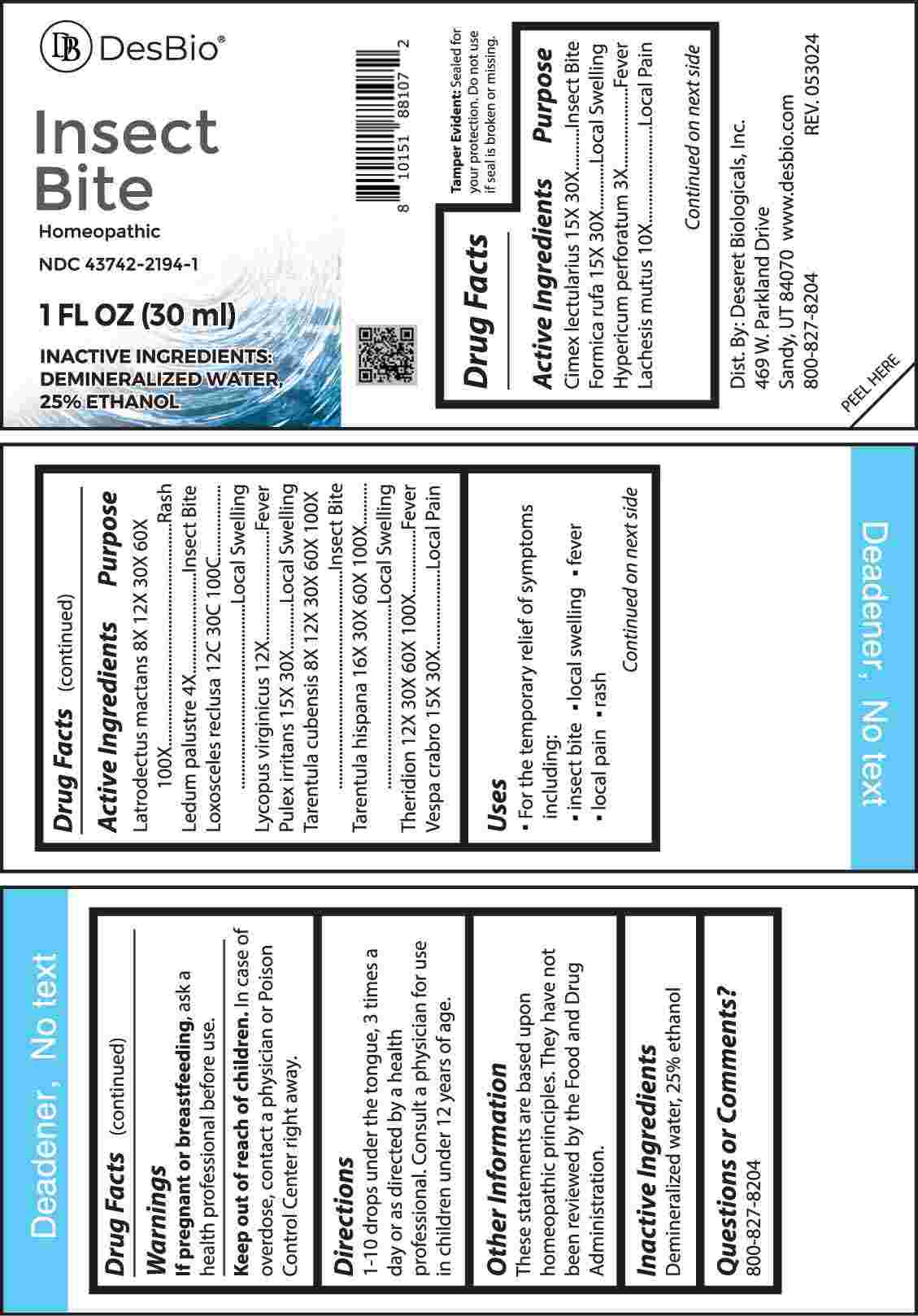 DRUG LABEL: Insect Bite
NDC: 43742-2194 | Form: LIQUID
Manufacturer: Deseret Biologicals, Inc.
Category: homeopathic | Type: HUMAN OTC DRUG LABEL
Date: 20241106

ACTIVE INGREDIENTS: CIMEX LECTULARIUS 15 [hp_X]/1 mL; FORMICA RUFA 15 [hp_X]/1 mL; PULEX IRRITANS WHOLE 15 [hp_X]/1 mL; VESPA CRABRO 15 [hp_X]/1 mL; HYPERICUM PERFORATUM WHOLE 3 [hp_X]/1 mL; LACHESIS MUTA VENOM 10 [hp_X]/1 mL; LATRODECTUS MACTANS 8 [hp_X]/1 mL; RHODODENDRON TOMENTOSUM LEAFY TWIG 4 [hp_X]/1 mL; LOXOSCELES RECLUSA 12 [hp_C]/1 mL; LYCOPUS VIRGINICUS WHOLE 12 [hp_X]/1 mL; CITHARACANTHUS SPINICRUS 8 [hp_X]/1 mL; LYCOSA TARANTULA 16 [hp_X]/1 mL; THERIDION CURASSAVICUM 12 [hp_X]/1 mL
INACTIVE INGREDIENTS: WATER; ALCOHOL

DRUG FACTS:

ACTIVE INGREDIENTS:

Cimex Lectularius 15X, 30X, Formica Rufa 15X, 30X, Hypericum Perforatum 3X, Lachesis Mutus 10X, Latrodectus Mactans 8X, 12X, 30X, 60X, 100X, Ledum Palustre 4X, Loxosceles Reclusa 12C, 30C, 100C, Lycopus Virginicus 12X, Pulex Irritans 15X, 30X, Tarentula Cubensis 8X, 12X, 30X, 60X, 100X, Tarentula Hispana 16X, 30X, 60X, 100X, Theridion 12X, 30X, 60X, 100X, Vespa Crabro 15X, 30X.

PURPOSE:

Cimex Lectularius – Insect Bite, Formica Rufa – Local Swelling, Hypericum Perforatum - Fever, Lachesis Mutus – Local Pain, Latrodectus Mactans - Rash, Ledum Palustre – Insect Bite, Loxosceles Reclusa – Local Swelling, Lycopus Virginicus - Fever, Pulex Irritans – Local Swelling, Tarentula Cubensis – Insect Bite, Tarentula Hispana – Local Swelling, Theridion - Fever, Vespa Crabro – Local Pain

USES:

• For the temporary relief of symptoms including:

• insect bites • local swelling • fever • local pain • rash

These statements are based upon homeopathic principles. They have not been reviewed by the Food and Drug Administration.

WARNINGS:

If pregnant or breast-feeding, ask a health professional before use.

Keep out of reach of children. In case of overdose, contact a physician or Poison Control Center right away.

Tamper Evident: Sealed for Your Protection. Do not use if seal is broken or missing.

KEEP OUT OF REACH OF CHILDREN:

In case of overdose, contact a physician or Poison Control Center right away.

DIRECTIONS:

1-10 drops under the tongue, 3 times a day or as directed by a health professional. Consult a physician for use in children under 12 years of age.

INACTIVE INGREDIENTS:

Demineralized water, 25% ethanol

QUESTIONS:

Dist. By: Deseret Biologicals, Inc.
469 W. Parkland Drive
Sandy, UT 84070

www.desbio.com

800-827-8204

PACKAGE LABEL DISPLAY:

DesBio

Insect Bite

Homeopathic

NDC 43742-2194-1

1 FL OZ (30 ml)